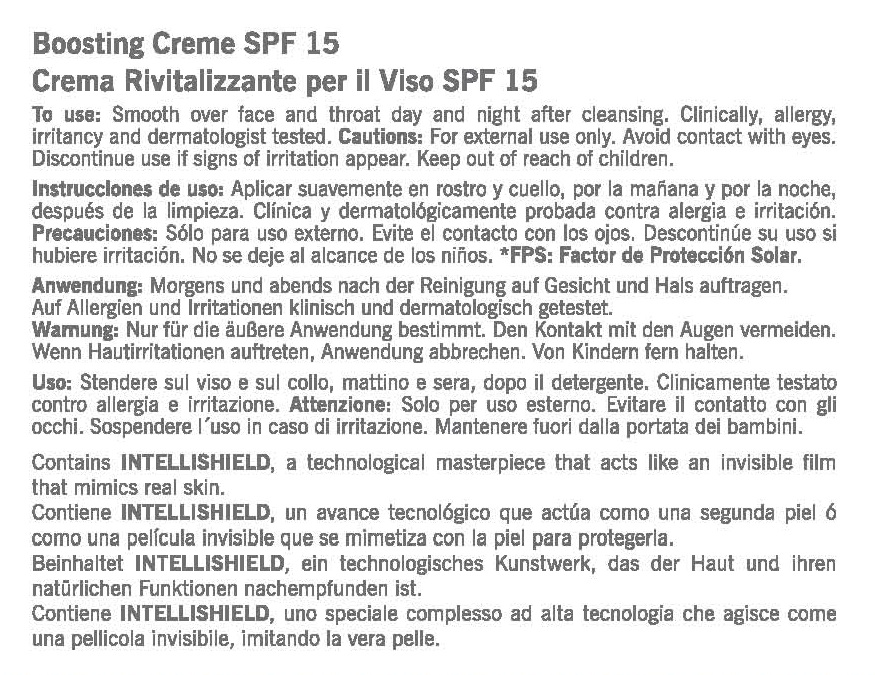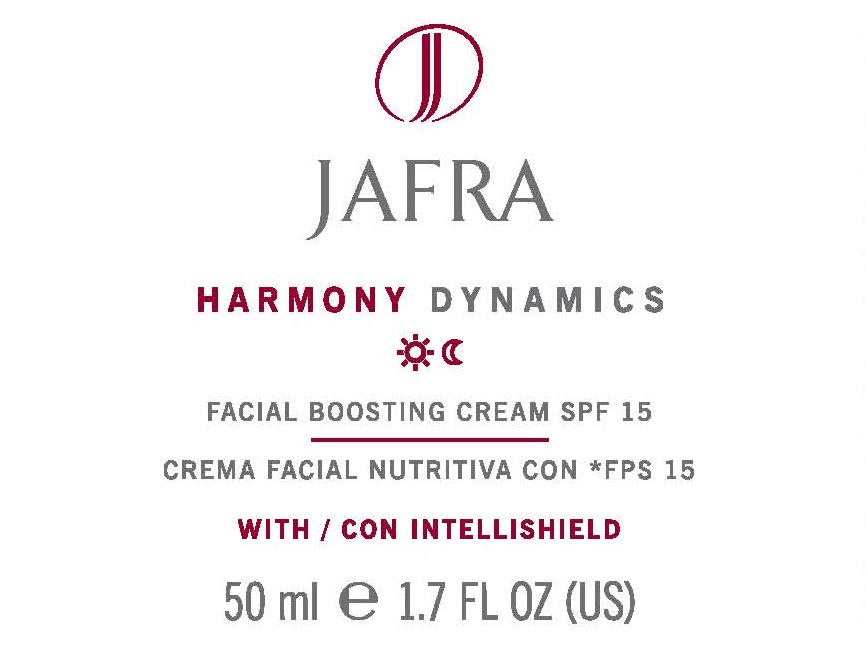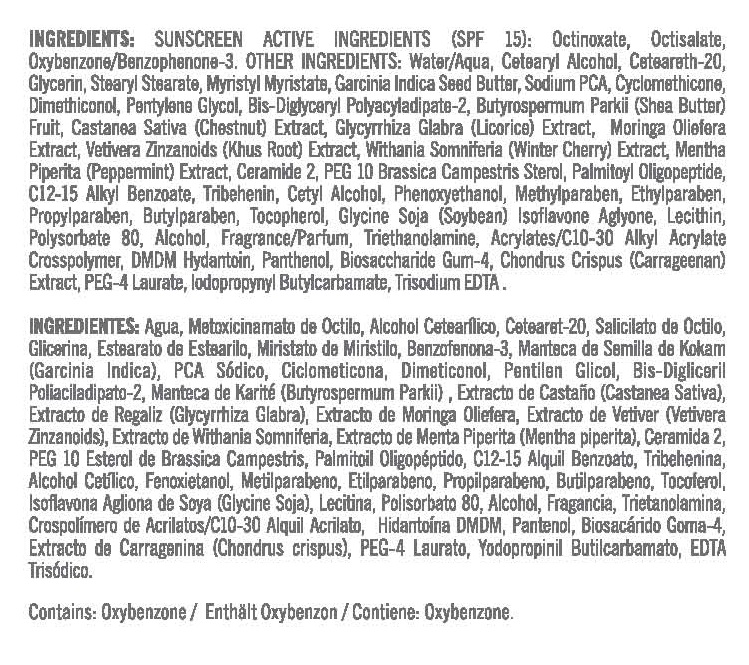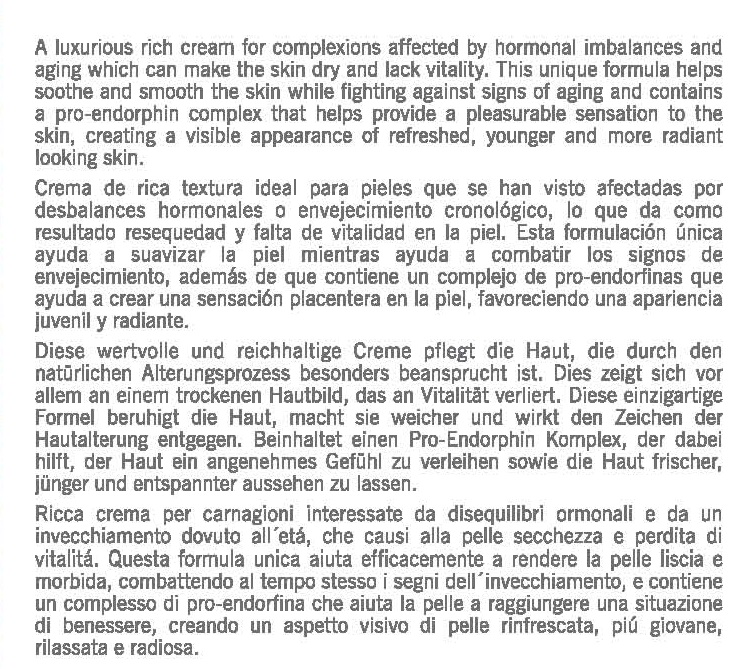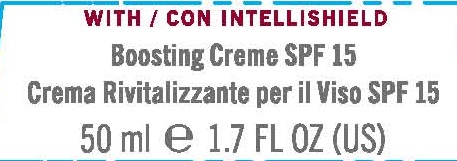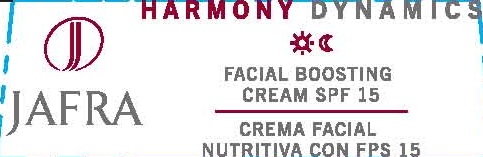 DRUG LABEL: HARMONY DYNAMICS FACIAL BOOSTING
NDC: 68828-163 | Form: CREAM
Manufacturer: JAFRA COSMETICS INTERNATIONAL
Category: otc | Type: HUMAN OTC DRUG LABEL
Date: 20120531

ACTIVE INGREDIENTS: OCTINOXATE 7 g/100 mL; OCTISALATE 4 g/100 mL; OXYBENZONE 2 g/100 mL
INACTIVE INGREDIENTS: WATER; CETOSTEARYL ALCOHOL; POLYOXYL 20 CETOSTEARYL ETHER; GLYCERIN; STEARYL STEARATE; MYRISTYL MYRISTATE; GARCINIA INDICA SEED BUTTER; SODIUM PYRROLIDONE CARBOXYLATE; CYCLOMETHICONE; DIMETHICONOL (250000 MW); PENTYLENE GLYCOL; DIGLYCERIN; SHEA BUTTER; SPANISH CHESTNUT; LICORICE; MORINGA OLEIFERA LEAF; VETIVERIA ZIZANIOIDES ROOT; WITHANIA SOMNIFERA LEAF; PEPPERMINT; CERAMIDE 2; CAMPESTEROL; PALMITOYL OLIGOPEPTIDE; ALKYL (C12-15) BENZOATE; TRIBEHENIN; CETYL ALCOHOL; PHENOXYETHANOL; METHYLPARABEN; ETHYLPARABEN; PROPYLPARABEN; BUTYLPARABEN; TOCOPHEROL; SOYBEAN; LECITHIN, SOYBEAN; POLYSORBATE 80; ALCOHOL; TROLAMINE; CARBOMER INTERPOLYMER TYPE A (55000 MPA.S); DMDM HYDANTOIN; PANTHENOL; BIOSACCHARIDE GUM-1; CHONDRUS CRISPUS; PEG-4 LAURATE; IODOPROPYNYL BUTYLCARBAMATE; EDETATE TRISODIUM

HARMONY DYNAMICS FACIAL BOOSTING CREAM SPF-15

SUNSCREEN ACTIVE INGREDIENT (SPF 15):
OCTINOXATE/ETHYLHEXYL METHOXYCINNAMATE, OCTISALATE/ETHYLHEXYL SALICYLATE, OXYBENZONE/BENZOPHENONE-3

PURPOSE: SUNSCREEN

INACTIVE INGREDIENT

INGREDIENTS: WATER/AQUA, CETEARYL ALCOHOL, CETEARETH-20, GLYCERIN, STEARYL STEARATE, MYRISTYL MYRISTATE, GARCINIA INDICA SEED BUTTER, SODIUM PCA, CYCLOMETHICONE, DIMETHICONOL, PENTYLENE GLYCOL, BIS-DIGLYCERYL POLYACRYLADIPATE-2, BUTYROSPERMUM PARKII (SHEA BUTTER) FRUIT, CASTANEA SATIVA (CHESTNUT) EXTRACT, GLYCYRRHIZA GLABRA (LICORICE) EXTRACT, MORINGA OLIEFERA EXTRACT, VETIVERA ZINZANOIDS (KHUS ROOT) EXTRACT, WITHANIA SOMNIFERIA (WINTER CHERRY) EXTRACT, MENTHA PIPERTITA (PEPPERMINT) EXTRACT, CERAMIDE 2, PEG 10 BRASSICA CAMESTRIS STEROL, PALMITOYL OLIGOPEPTIDE, C12-15 ALKYL BENZOATE, TRIBEHENIN, CETYL ALCOHOL, PHENOXYETHANOL, METHYLPARABEN, ETHYLPARABEN, PROPYLPARABEN, BUTYLPARABEN, TOCOPHEROL, GLYCEINE SOJA (SOYBEAN) ISOFLAVONE AGLYONE, LECITHIN, POLYSORBATE 80, ALCOHOL, FRAGRANCE/PARFUM, TRIETHANOLAMINE, ACRYLATES/C10-30 ALKYL ACRYLATE CROSSPOLYMER, DMDM HYDANTOIN, PANTHENOL, BIOSACCHARIDE GUM-4, CHONDRUS CRISPUS (CARRAGEENAN) EXTRACT, PEG-4 LAURATE, IODOPROPYL BUTYLCARBAMATE, TRISODIUM EDTA.

DESCRIPTION

A LUXURIOUS RICH CREAM FOR COMPLEXIONS AFFECTED BY HORMONAL IMBALANCES AND AGING WHICH CAN MAKE THE SKIN DRY AND LACK VITALITY.

INDICATIONS AND USAGE

THIS UNIQUE FORMULA HELPS SOOTHE AND SMOOTH THE SKIN WHILE FIGHTING AGAINST SIGNS OF AGING AND CONTAINS A PRO-ENDORPHIN COMPLEX THAT HELPS PROVIDE A PLEASURABLE SENSATION TO THE SKIN, CREATING A VISIBLE APPEARANCE OF REFRESHED, YOUNGER AND MORE RADIANT LOOKING SKIN.

INSTRUCTIONS FOR USE

TO USE: SMOOTH OVER FACE AND THROAT DAY AND NIGHT AFTER CLEANSING.

WARNINGS

CAUTION: FOR EXTERNAL USE ONLY. AVOID CONTACT WITH EYES.

DISCONTINUE USE IF SIGNS OF IRRITATION APPEAR.

KEEP OUT OF REACH OF CHILDREN.

OTHER SAFETY INFORMATION

CLINICALLY, ALLERGY, IRRITANCY AND DERMATOLOGIST TESTED.

PACKAGE LABEL

JAFRA

HARMONY DYNAMICS

FACIAL BOOSTING CREAM SPF 15

WITH / CON INTELLISHIELD